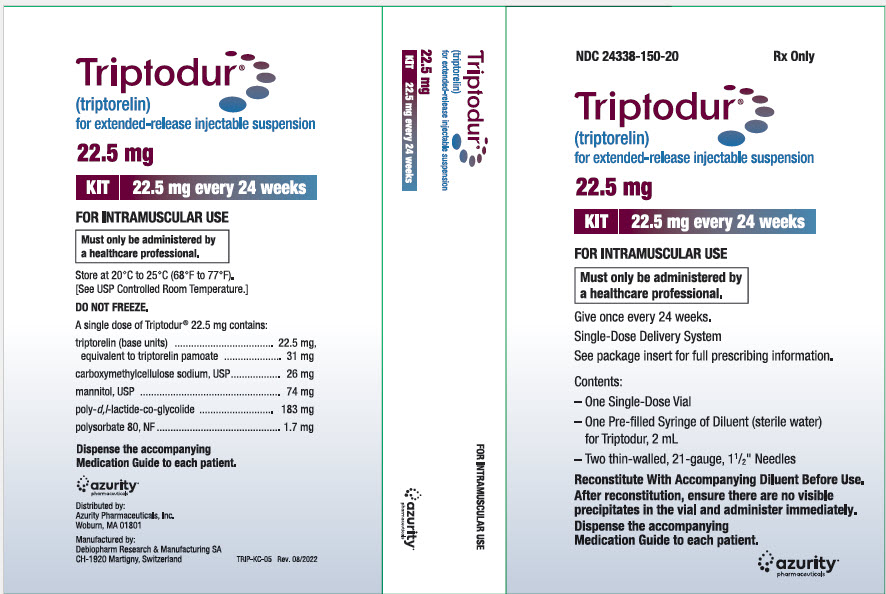 DRUG LABEL: TRIPTODUR
NDC: 59368-404 | Form: KIT | Route: INTRAMUSCULAR
Manufacturer: Praxis, LLC
Category: prescription | Type: HUMAN PRESCRIPTION DRUG LABEL
Date: 20230101

ACTIVE INGREDIENTS: TRIPTORELIN 22.5 mg/2 mL
INACTIVE INGREDIENTS: POLY(DL-LACTIC-CO-GLYCOLIC ACID), (50:50; 12000 MW); MANNITOL; CARBOXYMETHYLCELLULOSE SODIUM, UNSPECIFIED; POLYSORBATE 80; WATER

TRIPTODUR (triptorelin) for extended-release injectable suspension, for intramuscular use

7 DRUG INTERACTIONS

7.1 Drug-Drug Interactions

Results of in vitrostudies show that drug-drug interactions with triptorelin are unlikely [see Clinical Pharmacology (12.3)]. However, in the absence of relevant data and as a precaution, hyperprolactinemic drugs should not be used concomitantly with triptorelin since hyperprolactinemia reduces the number of pituitary GnRH receptors.

7.2 Drug-Laboratory Test Interactions

Administration of TRIPTODUR results in suppression of the pituitary-gonadal system.

The effect of TRIPTODUR on pituitary and gonadal function is expected to disappear within six to twelve months after treatment discontinuation. Therefore, diagnostic tests of pituitary gonadotropic and gonadal functions conducted during treatment or after discontinuation of treatment may be affected.

8 USE IN SPECIFIC POPULATIONS

8.1 Pregnancy

Risk Summary

TRIPTODUR is contraindicated in women who are pregnant [see Contraindications (4)] since expected hormonal changes that occur with TRIPTODUR treatment increase the risk for pregnancy loss. Available data with triptorelin use in pregnant women are insufficient to determine a drug-associated risk of adverse developmental outcomes. Based on mechanism of action in humans and findings of increased pregnancy loss in animal studies, TRIPTODUR may cause fetal harm when administered to pregnant women. Advise pregnant women of the potential risk to a fetus.

The estimated background risk of major birth defects and miscarriage for the indicated population is unknown. In the US general population, the estimated background risk of major birth defects and miscarriage in clinically recognized pregnancies is 2% - 4% and 15% -20%, respectively.

Data

Animal Data

In pregnant rats administered triptorelin at doses of 2, 10, and 100 mcg/kg/day during the period of organogenesis, maternal toxicity (decrease in body weight) and embryo-fetal toxicities (pre-implantation loss, increased resorption, and reduced number of viable fetuses) were observed at 100 mcg/kg, approximately 4 times the clinical dose based on body surface area. No embryonic and fetal developmental toxicities were observed in mice at doses up to 4 times the clinical dose. Teratogenic effects were not observed in viable fetuses in rats or mice.

8.2 Lactation

Risk Summary

There are no data on the presence of triptorelin in human milk, or the effects of the drug on the breastfed infant, or on milk production. The developmental and health benefits of breastfeeding should be considered along with the mother's clinical need for TRIPTODUR and any potential adverse effects on the breastfed child from TRIPTODUR or from the underlying maternal condition.

8.4 Pediatric Use

The safety and effectiveness of TRIPTODUR have been established in pediatric patients 2 years of age and older based on a single-arm open-label study of 44 children 2-9 years of age with CPP [see Clinical Studies (14)] . The safety and effectiveness of TRIPTODUR have not been established in pediatric patients less than 2 years old.

8.6 Renal Impairment

TRIPTODUR has not been studied in children with renal impairment. Adult subjects with renal impairment had higher exposure than young healthy adult males [see Clinical Pharmacology (12.3)].

8.7 Hepatic Impairment

TRIPTODUR has not been studied in children with hepatic impairment. Adult subjects with hepatic impairment had higher exposure than young healthy adult males [see Clinical Pharmacology (12.3)].

10 OVERDOSAGE

There is no experience with overdosage in clinical trials of triptorelin. If overdosage occurs, therapy should be discontinued and appropriate supportive and symptomatic treatment administered.

12 CLINICAL PHARMACOLOGY

12.1 Mechanism of Action

Triptorelin is a GnRH agonist.

12.2 Pharmacodynamics

Following the first administration, there is a transient surge in circulating levels of LH, FSH, testosterone, and estradiol [see Warnings and Precautions (5.2)] . After chronic and continuous administration, by 4 weeks after initiation of therapy, a sustained decrease in LH and FSH secretion and marked reduction in sex steroids are observed.

12.3 Pharmacokinetics

Absorption

After an initial intramuscular TRIPTODUR 22.5 mg injection and a second 22.5 mg intramuscular injection 24 weeks later in children 2 to 9 years old with CPP, triptorelin peaked 4 hours postdose with a geometric mean Cmaxof 39.9 and 36.5 ng/mL, respectively. No apparent accumulation of triptorelin occurred after the second injection. Absorption occurred in two phases, a burst phase followed by a maintenance release phase. In children with CPP, following the burst phase after the first 22.5 mg injection, geometric mean serum triptorelin levels were 0.11, 0.17, 0.05 and 0.03 ng/mL at Months 1, 2, 3, and 6, respectively.

Distribution

There is no evidence that triptorelin, at clinically relevant concentrations, binds to plasma proteins.

Elimination

Metabolism

The metabolism of triptorelin in humans is unknown, but is unlikely to involve hepatic microsomal enzymes (cytochrome P450). Thus far no metabolites of triptorelin have been identified. Pharmacokinetic data suggest that C-terminal fragments produced by tissue degradation are either completely degraded in the tissues, or rapidly degraded in plasma, or cleared by the kidneys.

Excretion

Triptorelin is eliminated by both the liver and the kidneys. Following intravenous administration of 0.5 mg triptorelin peptide to six healthy male volunteers with a creatinine clearance of 149.9 mL/min, 41.7% of the dose was excreted in urine as intact peptide with a total triptorelin clearance of 211.9 mL/min. This percentage increased to 62.3% in patients with liver disease who have a lower creatinine clearance (89.9 mL/min). It has also been observed that the nonrenal clearance of triptorelin (patient anuric, Clcreat= 0) was 76.2 mL/min, thus indicating that the nonrenal elimination of triptorelin is mainly dependent on the liver.

Specific Populations

Renal Impairment

After intravenous bolus injection of 0.5 mg triptorelin in adults, the two distribution half-lives were unaffected by renal impairment. However, renal insufficiency led to a decrease in total triptorelin clearance proportional to the decrease in creatinine clearance as well as increases in volume of distribution and consequently, an increase in the elimination half-life. Adult male subjects with moderate or severe renal impairment had approximately 2-fold higher exposure (AUC values) than young healthy adult males (see Table 1) [see Use in Specific Populations (8.6)].

Hepatic Impairment

After intravenous bolus injection of 0.5 mg triptorelin in adults, the two distribution half-lives were unaffected by hepatic impairment. In adult males with hepatic insufficiency, triptorelin clearance was reduced and exposure (AUC) was increased 3.7-fold compared to young healthy adult males (Table 2) [see Use in Specific Populations (8.7)] .

Table 2: Pharmacokinetic Parameters (Mean ± SD) in Healthy Adults, Adults with Renal Impairment, and Adults with Hepatic Impairment Following an I.V. Bolus of 0.5 mg Triptorelin in Solution
Group | Cmax (ng/mL) | AUCinf (h∙ng/mL) | Clp (mL/min) | Clrenal (mL/min) | t1/2(h) | Clcreat (mL/min)
6 healthy male volunteers | 48.2 ±11.8 | 36.1 ±5.8 | 211.9 ±31.6 | 90.6 ±35.3 | 2.81 ±1.21 | 149.9 ±7.3
6 males with moderate renal impairment | 45.6 ±20.5 | 69.9 ±24.6 | 120.0 ±45.0 | 23.3 ±17.6 | 6.56 ±1.25 | 39.7 ±22.5
6 males with severe renal impairment | 46.5 ±14.0 | 88.0 ±18.4 | 88.6 ±19.7 | 4.3 ±2.9 | 7.65 ±1.25 | 8.9 ±6.0
6 males with liver disease | 54.1 ±5.3 | 131.9 ±18.1 | 57.8 ±8.0 | 35.9 ±5.0 | 7.58 ±1.17 | 89.9 ±15.1

Drug-Drug Interactions

In Vitro Assessment of Drug Interactions

Drug Metabolizing Enzyme Inhibition

Triptorelin did not inhibit CYP1A2, 2B6, 2C8, 2C9, 2C19 or 2D6, or CYP 3A4/5 at clinically relevant concentrations.

Drug Metabolizing Enzyme Induction

In fresh human hepatocytes from three human donors, triptorelin did not induce CYP1A2 or CYP3A4/5 activity.

Transporters

Triptorelin was a poor P-gp substrate and had no inhibitory effect toward P-gp.

13 NONCLINICAL TOXICOLOGY

13.1 Carcinogenesis, Mutagenesis, Impairment of Fertility

Carcinogenesis was evaluated in an 18-month study in mice and a 24-month study in rats. In rats, triptorelin doses of 120, 600, and 3000 mcg/kg given every 28 days (approximately 0.2, 0.8, and 4 times the estimated human monthly dose based on body surface area) resulted in increased mortality with a drug treatment period of 13 to 19 months. The incidences of benign and malignant pituitary tumors and histosarcomas were increased in a dose-related manner. There were no treatment-related tumors in mice at exposure up to 4-fold higher than the estimated human monthly dose based on body surface area.

Mutagenicity studies performed with triptorelin using bacterial and mammalian systems (in vitroAmes test and chromosomal aberration test in CHO cells and an in vivomouse micronucleus test) provided no evidence of mutagenic potential.

After 60 days of subcutaneous treatment followed by a minimum of four estrus cycles prior to mating, triptorelin at doses of 2, 20, and 200 mcg/kg (approximately 0.07, 0.7, and 7 times the estimated human daily dose based on body surface area) or two monthly injections as slow release microspheres (~20 mcg/kg/day) had no effect on the fertility or general reproductive function of female rats.

No studies were conducted to assess the effect of triptorelin on male fertility.

16 HOW SUPPLIED/STORAGE AND HANDLING

Each TRIPTODUR 22.5 mg single-use kit (NDC 24338-150-20) contains:

- One single-dose vial of TRIPTODUR 22.5 mg (NDC 24338-150-01) with a Flip-Off seal containing sterile lyophilized white to slightly yellow powder cake
- One sterile, glass syringe with Luer Lock prefilled with 2 mL of Sterile Water for Injection (NDC 24338-150-02)
- Two sterile 21 gauge, 1½" needles (thin-wall) with safety cover
- One Package Insert

STORAGE AND HANDLING

Store at 20 to 25°C (68 to 77°F) excursions permitted to 15°C to 30°C (59°F to 86°F) [see USP Controlled Room Temperature]. Do not freeze.

17 PATIENT COUNSELING INFORMATION

Advise the patient to read the FDA-approved patient labeling (Patient Information and Medication Guide).

Hypersensitivity Reactions

Inform caregivers that anaphylactic shock, hypersensitivity, and angioedema have been reported with triptorelin use and to immediately seek medical attention if any hypersensitivity reaction occurs.

Symptoms after Initial TRIPTODUR Administration

Inform caregivers that during the first weeks after the first TRIPTODUR injection, signs of puberty may occur such as vaginal bleeding [see Warnings and Precautions (5.1)and Adverse Reactions (6.1)] . Caregivers should notify the physician if these symptoms continue beyond the second month after TRIPTODUR administration.

Psychiatric Events

Inform caregivers that symptoms of emotional lability, such as crying, irritability, impatience, anger, and aggression have been observed in patients receiving GnRH agonists, including triptorelin. Alert caregivers to the possibility of development or worsening of psychiatric symptoms, including depression, during treatment with TRIPTODUR [see Warnings and Precautions (5.2)and Adverse Reactions (6.2)].

Convulsions

Inform caregivers that reports of convulsions have been observed in patients receiving GnRH agonists, including triptorelin. Patients with a history of seizures, epilepsy, cerebrovascular disorders, central nervous system anomalies or tumors, and patients on concomitant medications that have been associated with convulsions may be at increased risk [see Warnings and Precautions (5.3)].

Pseudotumor Cerebri (Idiopathic Intracranial Hypertension)

Inform patients and caregivers that reports of pseudotumor cerebri (idiopathic intracranial hypertension) have been observed in pediatric patients receiving GnRH agonists, including triptorelin. Monitor patients for signs and symptoms of pseudotumor cerebri, including headache, and vision issues such as blurred vision, double vision, loss of vision, pain behind the eye or pain with eye movement, ringing in the ears, dizziness, and nausea. Advise patients and caregivers to contact their healthcare provider if the patient develops any of these symptoms. [see Warnings and Precautions (5.4)] .

Pregnancy is Contraindicated

TRIPTODUR is contraindicated in pregnancy. If the patient becomes pregnant while taking the drug, the patient should be informed of the potential risk to fetus [see Use in Specific Populations (8.1)].

Compliance with the Dosing Schedule

Inform caregivers about the importance of adherence to the TRIPTODUR dosing schedule of one injection every 24 weeks. Patients should not miss or delay a scheduled dose.

Manufactured for:
Azurity Pharmaceuticals, Inc.
Woburn, MA 01801

Manufactured by:
Debiopharm Research & Manufacturing SA
CH-1920 Martigny, Switzerland

TRIPTODUR is a registered trademark of Debiopharm International SA.

Patent: https://azurity.com/patents_and_trademarks/

This product's labeling may have been updated. For current Full Prescribing Information, please visit www.triptodur.com

TRIP-PI-08 Rev. NOV 2023

PRINCIPAL DISPLAY PANEL - Kit Carton

NDC 24338-150-20
Rx Only

Triptodur®
(triptorelin)
for extended-release injectable suspension

22.5 mg

KIT
22.5 mg every 24 weeks

FOR INTRAMUSCULAR USE

Must only be administered by
a healthcare professional.

Give once every 24 weeks.
Single-Dose Delivery System
See package insert for full prescribing information.

Contents:

–One Single-Dose Vial

–One Pre-filled Syringe of Diluent (sterile water)
for Triptodur, 2 mL

–Two thin-walled, 21-gauge, 1½" Needles

Reconstitute With Accompanying Diluent Before Use.

After reconstitution, ensure there are no visible
precipitates in the vial and administer immediately.

Dispense the accompanying
Medication Guide to each patient.

azurity®
pharmaceuticals